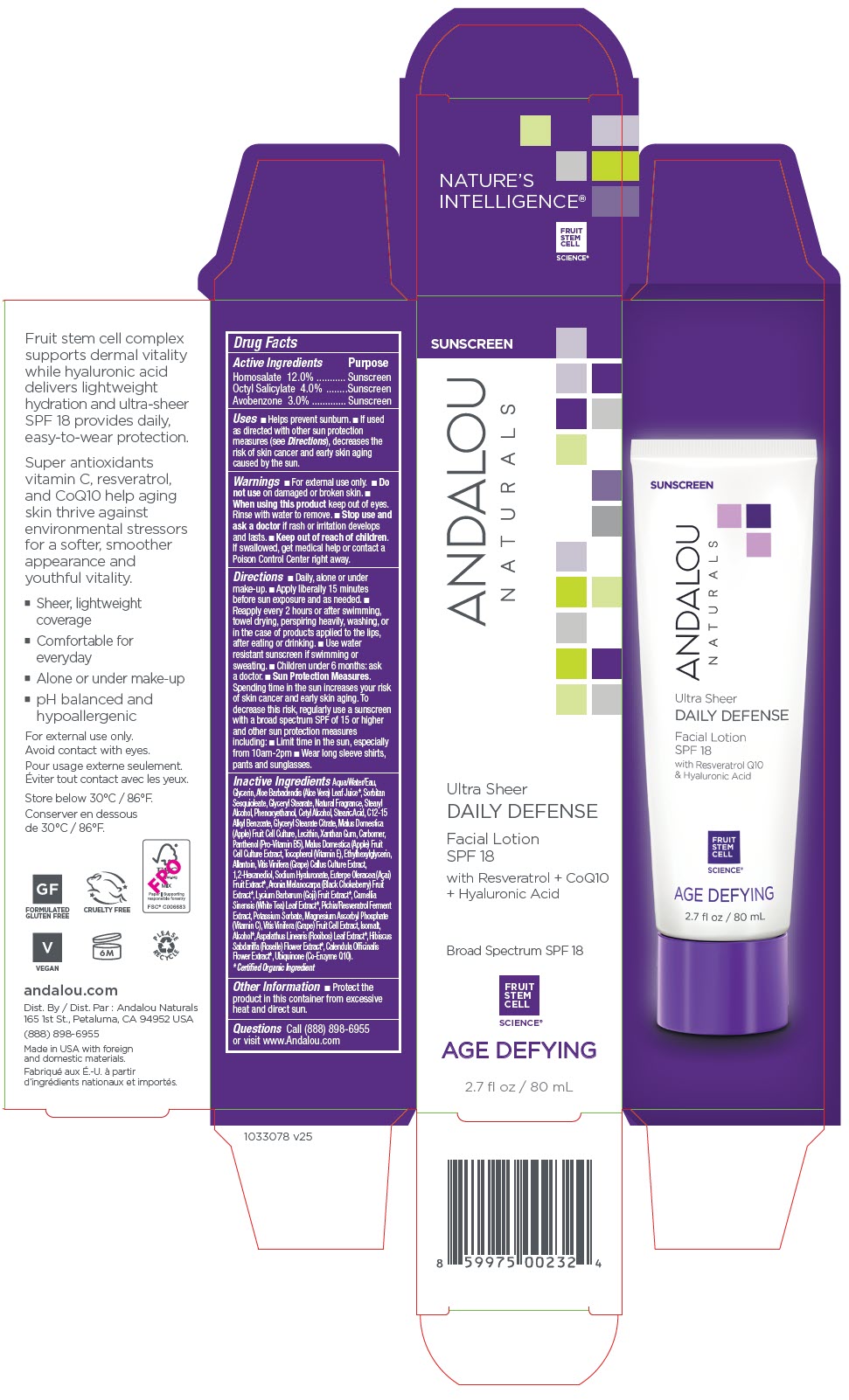 DRUG LABEL: ULTRA SHEER DAILY DEFENSE FACIAL SPF 18
NDC: 55560-3331 | Form: LOTION
Manufacturer: Andalou naturals
Category: otc | Type: HUMAN OTC DRUG LABEL
Date: 20250611

ACTIVE INGREDIENTS: HOMOSALATE 120 mg/1 mL; OCTISALATE 40 mg/1 mL; AVOBENZONE 30 mg/1 mL
INACTIVE INGREDIENTS: WATER; GLYCERIN; ALOE VERA LEAF; SORBITAN SESQUIOLEATE; GLYCERYL MONOSTEARATE; STEARYL ALCOHOL; PHENOXYETHANOL; CETYL ALCOHOL; STEARIC ACID; ALKYL (C12-15) BENZOATE; GLYCERYL STEARATE CITRATE; APPLE; SOYBEAN LECITHIN; XANTHAN GUM; CARBOMER HOMOPOLYMER, UNSPECIFIED TYPE; PANTHENOL; TOCOPHEROL; ETHYLHEXYLGLYCERIN; ALLANTOIN; VITIS VINIFERA HIGH TANNIN CULTIVAR FRUIT CELL LYSATE; 1,2-HEXANEDIOL; HYALURONATE SODIUM; ACAI; ARONIA MELANOCARPA FRUIT JUICE; LYCIUM BARBARUM FRUIT; TEA LEAF; RESVERATROL; POTASSIUM SORBATE; MAGNESIUM ASCORBYL PHOSPHATE; ISOMALT; ALCOHOL; ASPALATHUS LINEARIS LEAF; HIBISCUS SABDARIFFA FLOWER; CALENDULA OFFICINALIS FLOWER; UBIDECARENONE

ULTRA SHEER DAILY DEFENSE FACIAL SPF 18

Drug Facts

ACTIVE INGREDIENT

Active Ingredients | Purpose
Homosalate 12.0% | Sunscreen
Octyl Salicylate 4.0% | Sunscreen
Avobenzone 3.0% | Sunscreen

Uses

- Helps prevent sunburn.
- If used as directed with other sun protection measures (see Directions), decreases the risk of skin cancer and early skin aging caused by the sun.

Warnings

- For external use only.

- Do not use on damaged or broken skin.

- When using this product keep out of eyes. Rinse with water to remove.

- Stop use and ask a doctor if rash or irritation develops and lasts.

- Keep out of reach of children. If swallowed, get medical help or contact a Poison Control Center right away.

Directions

- Daily, alone or under make-up.
- Apply liberally 15 minutes before sun exposure and as needed.
- Reapply every 2 hours or after swimming, towel drying, perspiring heavily, washing, or in the case of products applied to the lips, after eating or drinking.
- Use water resistant sunscreen if swimming or sweating.
- Children under 6 months: ask a doctor.
- Sun Protection Measures. Spending time in the sun increases your risk of skin cancer and early skin aging. To decrease this risk, regularly use a sunscreen with a broad spectrum SPF of 15 or higher and other sun protection measures including:
  - Limit time in the sun, especially from 10am-2pm
  - Wear long sleeve shirts, pants and sunglasses.

Inactive Ingredients

Aqua/Water/Eau, Glycerin, Aloe Barbadendis (Aloe Vera) Leaf Juice [Certified Organic Ingredient] , Sorbitan Sesquioleate, Glyceryl Stearate, Natural Fragrance, Stearyl Alcohol, Phenoxyethanol, Cetyl Alcohol, Stearic Acid, C12-15 Alkyl Benzoate, Glyceryl Stearate Citrate, Malus Domestica (Apple) Fruit Cell Culture, Lecithin, Xanthan Gum, Carbomer, Panthenol (Pro-Vitamin B5), Malus Domestica (Apple) Fruit Cell Culture Extract, Tocopherol (Vitamin E), Ethylhexylglycerin, Allantoin, Vitis Vinifera (Grape) Callus Culture Extract, 1,2-Hexanediol, Sodium Hyaluronate, Euterpe Oleracea (Açai) Fruit Extract, Aronia Melanocarpa (Black Chokeberry) Fruit Extract, Lycium Barbarum (Goji) Fruit Extract, Camellia Sinensis (White Tea) Leaf Extract, Pichia/Resveratrol Ferment Extract, Potassium Sorbate, Magnesium Ascorbyl Phosphate (Vitamin C), Vitis Vinifera (Grape) Fruit Cell Extract, Isomalt, Alcohol, Aspalathus Linearis (Rooibos) Leaf Extract, Hibiscus Sabdariffa (Roselle) Flower Extract, Calendula Officinalis Flower Extract, Ubiquinone (Co-Enzyme Q10).

Other Information

- Protect the product in this container from excessive heat and direct sun.

Questions

Call (888) 898-6955 or visit www.Andalou.com

Dist. By: Andalou Naturals
165 1st St., Petaluma, CA 94952 USA

PRINCIPAL DISPLAY PANEL - 80 mL Tube Carton

SUNSCREEN

ANDALOU
NATURALS

Ultra Sheer
DAILY DEFENSE

Facial Lotion
SPF 18

with Resveratrol + CoQ10
+ Hyaluronic Acid

Broad Spectrum SPF 18

FRUIT
STEM
CELL
SCIENCE®

AGE DEFYING

2.7 fl oz / 80 mL